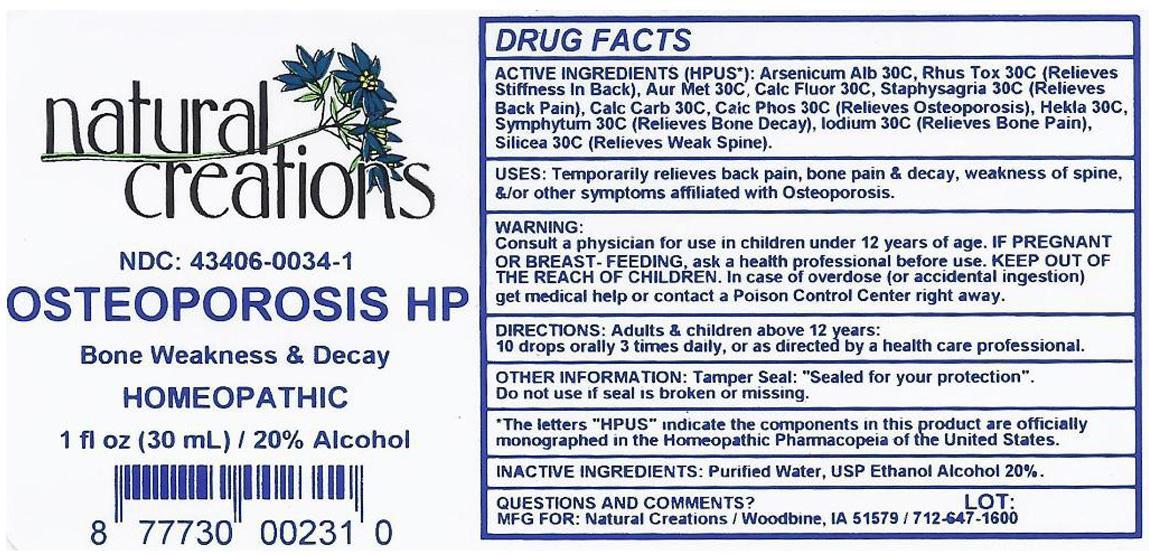 DRUG LABEL: OSTEOPOROSIS HP
NDC: 43406-0034 | Form: LIQUID
Manufacturer: Natural Creations, Inc.
Category: homeopathic | Type: HUMAN OTC DRUG LABEL
Date: 20121109

ACTIVE INGREDIENTS: ARSENIC TRIOXIDE 30 [hp_X]/1 mL; GOLD 30 [hp_X]/1 mL; OYSTER SHELL CALCIUM CARBONATE, CRUDE 30 [hp_X]/1 mL; CALCIUM FLUORIDE 30 [hp_X]/1 mL; CALCIUM PHOSPHATE 30 [hp_X]/1 mL; HYDROFLUORIC ACID 30 [hp_X]/1 mL; HEKLA LAVA 30 [hp_X]/1 mL; TOXICODENDRON PUBESCENS LEAF 30 [hp_X]/1 mL; SILICON DIOXIDE 30 [hp_X]/1 mL; DELPHINIUM STAPHISAGRIA SEED 30 [hp_X]/1 mL; COMFREY LEAF 30 [hp_X]/1 mL
INACTIVE INGREDIENTS: WATER; ALCOHOL

OSTEOPOROSIS HP

ACTIVE INGREDIENT

ACTIVE INGREDIENTS (HPUS*): Arsenicum Album 30X, Aurum Metallicum 30X, Calcarea Carbonica 30X, Calcarea Fluorica 30X, Calcarea Phosphorica 30X, Fluoricum Acidum 30X, Hekla Lava 30X, Rhus Toxicodendron 30X, Silicea 30X, Staphysagria 30X, Symphytum Officinale 30X

INDICATIONS AND USAGE

USES: Temporarily relieves back pain, bone pain & decay, weakness of spine, &/or other symptoms affiliate with Osteoporosis.

WARNING:

Consult a physician for use in children under 12 years of age. IF PREGNANT OR BREAST-FEEDING, ask a health care professional before use. KEEP OUT OF THE REACH OF CHILDREN. In case of overdose (or accidental ingestion) get medical help or contact a Poison Control center right away.

DOSAGE AND ADMINISTRATION

DIRECTIONS: Adults and children above 12 years: 10 drops orally 3 times daily, or as directed by a health care professional.

OTHER INFORMATION: Tamper Seal: "Sealed for your protection."

Do not use if seal is broken or missing.

REFERENCES

*The letters "HPUS" indicate the components in the product are officially monographed in the Homeopathic Pharmacopeia of the United States.

INACTIVE INGREDIENTS: Purified Water, USP Ethanol Alcohol 20%

QUESTIONS AND COMMENTS?
MFG FOR: Natural Creations / Woodbine, IA / 51579 712.647.1600

LOT:

PURPOSE

USES: Temporarily relieves back pain, bone pain & decay, weakness of spine, &/or other symptoms affiliated with Osteoporosis.

KEEP OUT OF REACH OF CHILDREN

KEEP OUT OF THE REACH OF CHILDREN. In case of overdose (or accidental ingestion) get medical help or contact a Poison Control Center.

PACKAGE LABEL

NDC: 43406-0034-1

OSTEOPOROSIS HP

Bone Weakness & Decay

HOMEOPATHIC

1 fl oz (30 mL) / 20% Alcohol

UPC: 877730002310